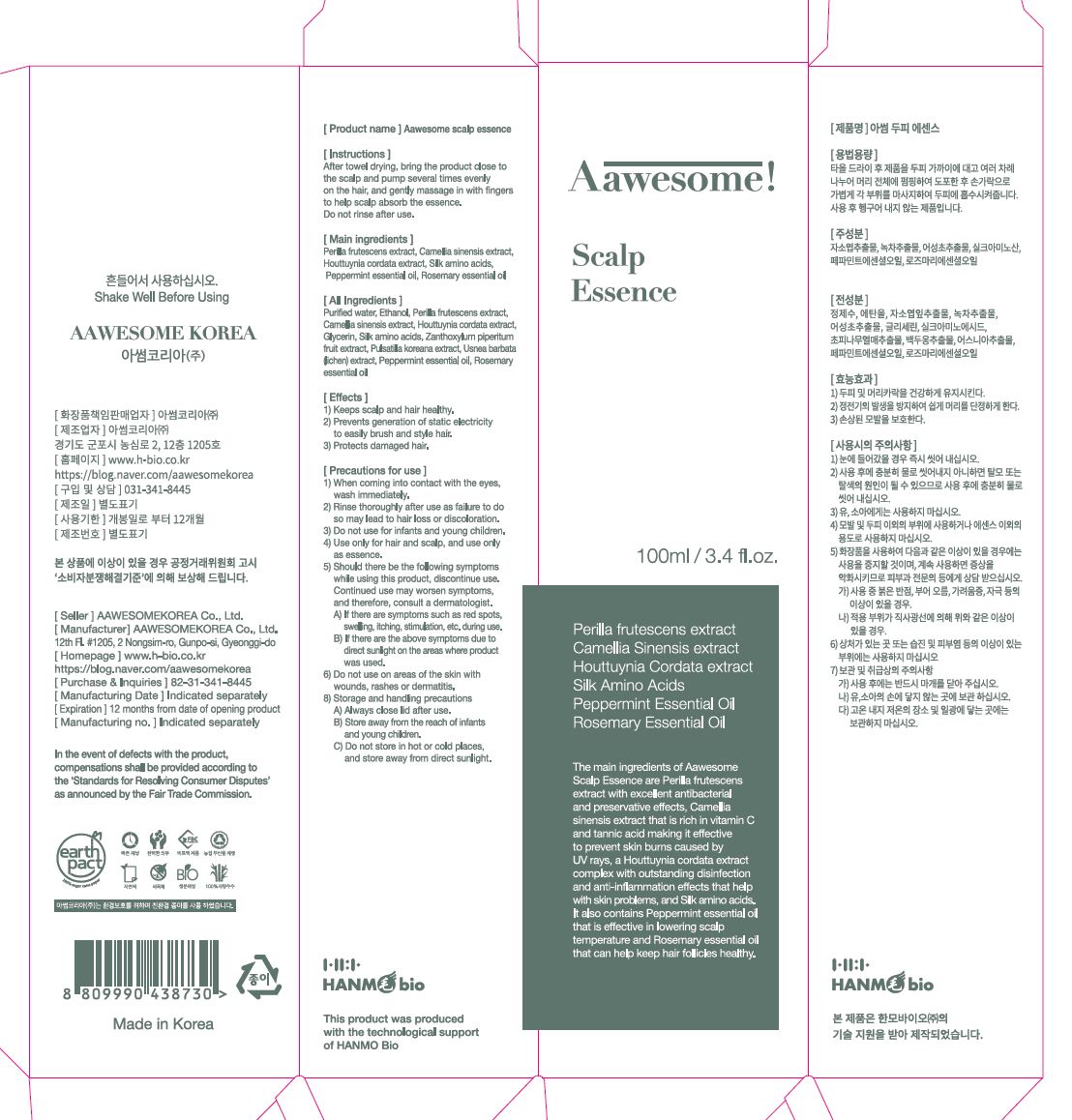 DRUG LABEL: AAWESOME SCALP ESSENCE
NDC: 82483-0003 | Form: SHAMPOO
Manufacturer: AAWESOMEKOREA Co., Ltd.
Category: otc | Type: HUMAN OTC DRUG LABEL
Date: 20220122

ACTIVE INGREDIENTS: CAMELLIA SINENSIS WHOLE 0.017 g/100 mL; PEPPERMINT OIL 0.1 g/100 mL; PERILLA FRUTESCENS WHOLE 0.017 g/100 mL; HOUTTUYNIA CORDATA WHOLE 0.017 g/100 mL; ROSEMARY OIL 0.1 g/100 mL; AMINO ACIDS, SILK 0.5 g/100 mL
INACTIVE INGREDIENTS: WATER

ACTIVE INGREDIENT

silk amino acid, CAMELLIA SINENSIS, PEPPERMINT, ROSEMARY, PERILLA FRUTESCENS, HOUTTUYNIA CORDATA

PURPOSE

keeps scalp and hair healthy

prevents generation of static electricity to easily brush and style hair

protects damaged hair

KEEP OUT OF REACH OF THE CHILDREN

WARNINGS

■ For external use only.

■ Do not use in eyes.

■ lf swallowed, get medical help promptly.

■ Stop use, ask doctor lf irritation occurs.

■ Keep out of reach of children.

DOSAGE AND ADMINISTRATION

for external use only

INACTIVE INGREDIENT

water, glycerin, etc

INDICATIONS AND USAGE

after towel drying, bring the product close to the scalp and pump several times evenly on the hair, and getly massage in with fingers to healp scalp absorb the essence

do not rinse after use